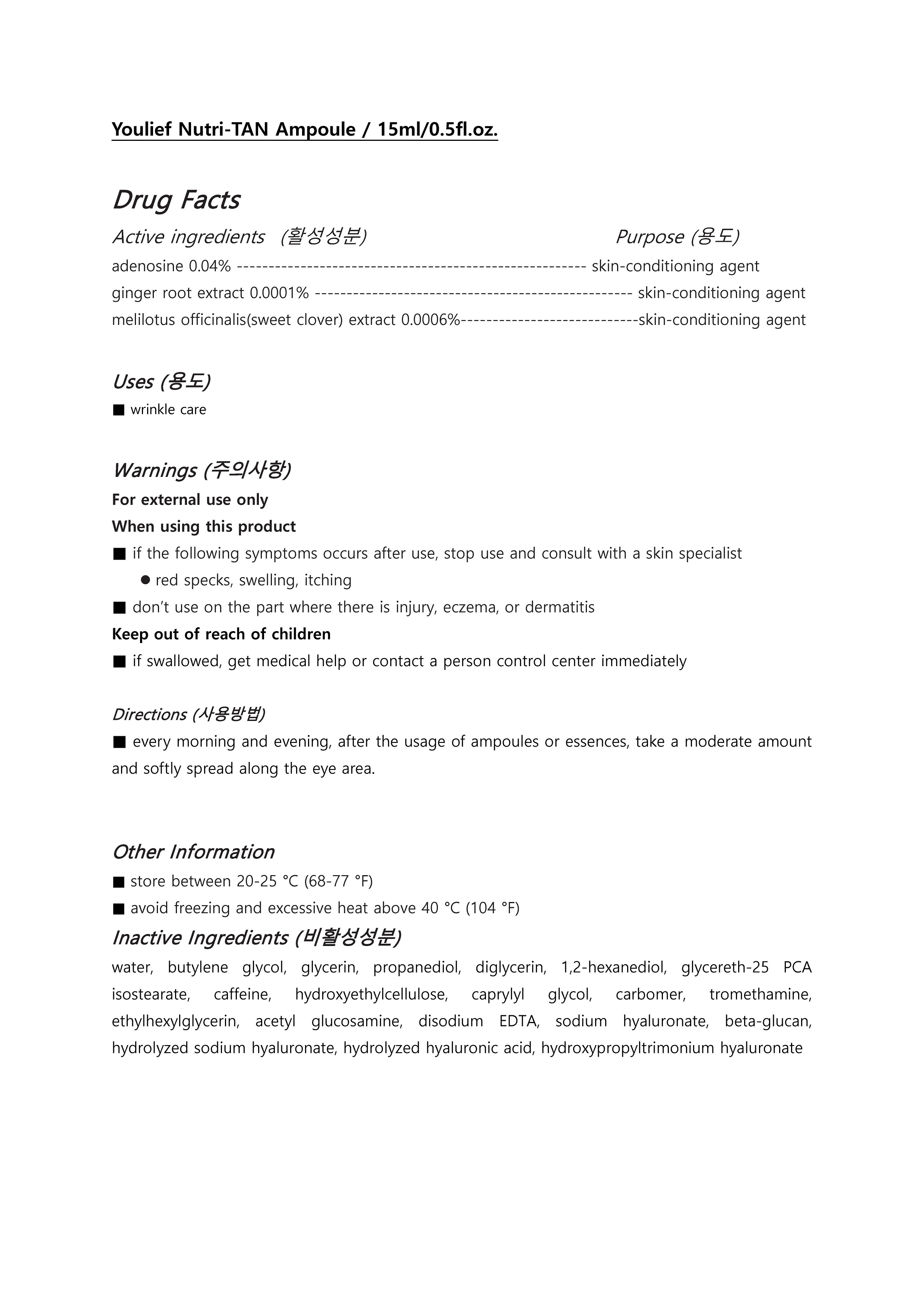 DRUG LABEL: Youlief Nutri-TAN Ampoule
NDC: 73560-0003 | Form: LIQUID
Manufacturer: Plcoskin
Category: otc | Type: HUMAN OTC DRUG LABEL
Date: 20200127

ACTIVE INGREDIENTS: MELILOTUS OFFICINALIS TOP 0.0006 g/100 mL; ADENOSINE 0.04 g/100 mL; GINGER 0.0001 g/100 mL
INACTIVE INGREDIENTS: WATER; BUTYLENE GLYCOL

Drug Facts

ACTIVE INGREDIENT

Adenosine, melilotus officinalis (sweet clover) extract, zingiberofficinale (ginger) root extract

INACTIVE INGREDIENT

water, butylene glycol, etc.

PURPOSE

anti-wrinkle

keep out of reach of the children

INDICATIONS AND USAGE

At the end of skin care, take a moderate amount of the contents and softly spread along the skin. Gently pat the skin where has wrinkles and lack of elasticity.

WARNINGS

For external use only
When using this product

■ if the following symptoms occurs after use, stop use and consult with a skin specialist

red specks, swelling, itching

■ don’t use on the part where there is injury, eczema, or dermatitis

Keep out of reach of children

■ if swallowed, get medical help or contact a person control center immediately

DOSAGE AND ADMINISTRATION

for external use only